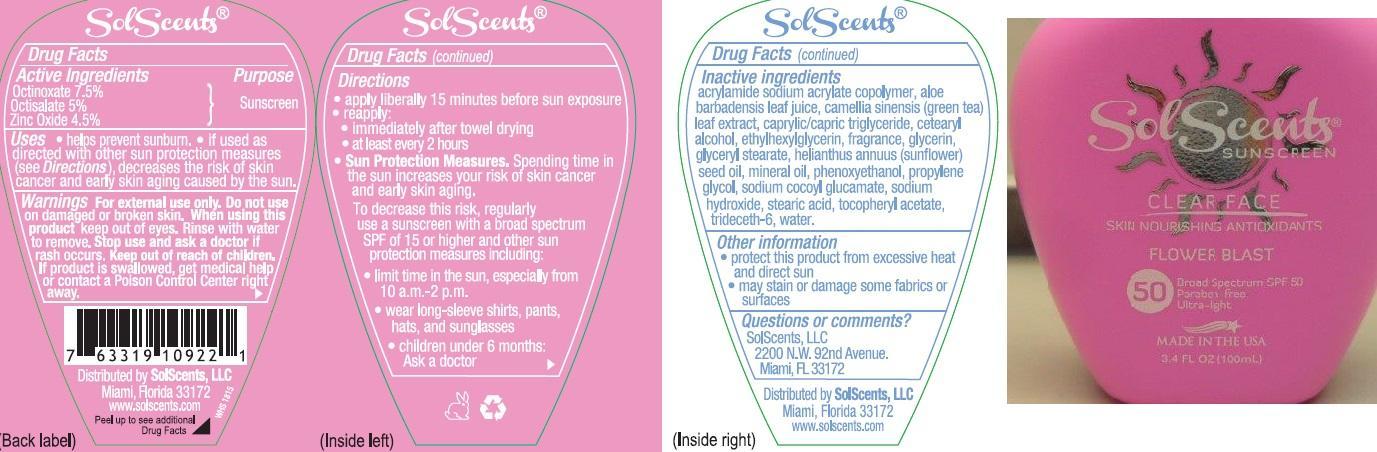 DRUG LABEL: SolScents
NDC: 58443-0175 | Form: LOTION
Manufacturer: Prime Enterprises, Inc.
Category: otc | Type: HUMAN OTC DRUG LABEL
Date: 20200117

ACTIVE INGREDIENTS: OCTINOXATE 76.5 mg/1 mL; OCTISALATE 51 mg/1 mL; ZINC OXIDE 45.9 mg/1 mL
INACTIVE INGREDIENTS: SODIUM HYDROXIDE; STEARIC ACID; .ALPHA.-TOCOPHEROL ACETATE; TRIDECETH-6; WATER; CAPRYLIC/CAPRIC MONO/DIGLYCERIDES; SODIUM ACRYLOYLDIMETHYLTAURATE-ACRYLAMIDE COPOLYMER (1:1; 90000-150000 MPA.S); ALOE VERA LEAF; GREEN TEA LEAF; CETOSTEARYL ALCOHOL; ETHYLHEXYLGLYCERIN; GLYCERIN; GLYCERYL STEARATE SE; SUNFLOWER SEED OIL GLYCERETH-8 ESTERS; MINERAL OIL; PHENOXYETHANOL; PROPYLENE GLYCOL; SODIUM COCOYL GLUTAMATE

Active ingredients

Octinozate 7.5% ,Octisalate 5%, and Zinc Oxide 4.5%

Purpose

Sunscreen

Uses

- Helps prevent sunburn. • If used as directed with other sun protection measures (See Directions), decreases the risk of skin cancer and early skin aging caused by the sun.

Warnings

OTHER SAFETY INFORMATION

For external use only.

Do not use on damaged or broken skin.

When using this product keep out of eyes. Rinse with water to remove.

Stop use and ask a doctor if rash occurs.

Keep out of reach of children. If product is swallowed, get medical help or contact a Poison Control Center right away.

Directions:

- apply liberally 15 minutes before sun exposure
- reapply:
- immediately after towel drying
- at least every 2 hours
- Sun Protection Measures: Spending time in the sun increases your risk of skin cancer & early skin aging. To decrease this risk, regularly use a sunscreen with a broad spectrum SPF of 15 or higher & other sun protection measures including:
- limit time in the sun, especially from 10 a.m. – 2 p.m.
- wear long sleeve shirts, pants, hats, and sunglasses
- Children under 6 months: Ask a doctor

Inactive Ingredients

acrylamide sodium acrylate copolymer, aloe barbadensis leaf juice, camellia sinensis (green tea) leaf extract, caprylic/capric tiglyceride, cetearyl alcohol, ethylhexylglycerin, fragrance, glycerin, glyceryl stearate, helianthus annuus (sunflower) seed oil, mineral oil, phenoxyethanol, propylene glycol, sodium cocoyl glucamate, sodium hydroxide, stearic acid, tocopheryl acetate, trideceth-6, water.

Other information

- protect this product from excessive heat and direct sun
- may stain or damage some fabrics or sufaces

Questions or comments?

SolScents, LLC

2200 N.W. 92nd Avenue.

Miami, FL 33172

PRINCIPAL DISPLAY PANEL - 100 mL Bottle Label

SolScents

SUNSCREEN

CLEAR FACE

SKIN NOUISHING ANTIOXIDANTS

FLOWER BLAST

50

Broad Spectrum SPF50

Paraben Free

Ultra-light

MADE IN TE USA

3.4 FL OZ (100 mL)